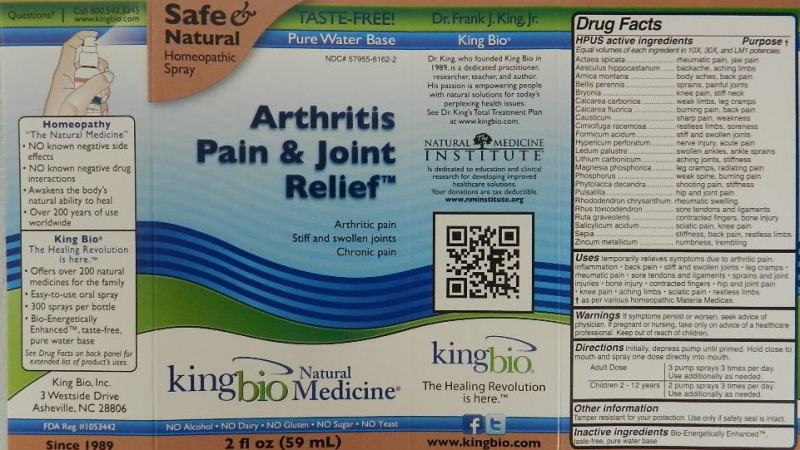 DRUG LABEL: Arthritis Pain and Joint Relief
NDC: 57955-6162 | Form: LIQUID
Manufacturer: King Bio Inc.
Category: homeopathic | Type: HUMAN OTC DRUG LABEL
Date: 20111117

ACTIVE INGREDIENTS: ACTAEA SPICATA ROOT 10 [hp_X]/59 mL; HORSE CHESTNUT 10 [hp_X]/59 mL; ARNICA MONTANA 10 [hp_X]/59 mL; BELLIS PERENNIS 10 [hp_X]/59 mL; BRYONIA ALBA ROOT 10 [hp_X]/59 mL; OYSTER SHELL CALCIUM CARBONATE, CRUDE 10 [hp_X]/59 mL; CALCIUM FLUORIDE 10 [hp_X]/59 mL; CAUSTICUM 10 [hp_X]/59 mL; BLACK COHOSH 10 [hp_X]/59 mL; FORMIC ACID 10 [hp_X]/59 mL; HYPERICUM PERFORATUM 10 [hp_X]/59 mL; LEDUM PALUSTRE TWIG 10 [hp_X]/59 mL; LITHIUM CARBONATE 10 [hp_X]/59 mL; MAGNESIUM PHOSPHATE, DIBASIC TRIHYDRATE 10 [hp_X]/59 mL; PHOSPHORUS 10 [hp_X]/59 mL; PHYTOLACCA AMERICANA ROOT 10 [hp_X]/59 mL; PULSATILLA VULGARIS 10 mL/59 mL; RHODODENDRON AUREUM LEAF 10 [hp_X]/59 mL; TOXICODENDRON PUBESCENS LEAF 10 [hp_X]/59 mL; RUTA GRAVEOLENS FLOWERING TOP 10 [hp_X]/59 mL; SALICYLIC ACID 10 [hp_X]/59 mL; SEPIA OFFICINALIS JUICE 10 [hp_X]/59 mL; ZINC 10 [hp_X]/59 mL
INACTIVE INGREDIENTS: WATER

Arthritis Pain and Joint Relief

Active Ingredients

HPUS active ingredients

Equal volumes of each ingredient in 10X, 30X, and LM1 potencies

Actaea spicata

Aesculus hippocastanum

Arnica montana

Bellis perennis

Bryonia

Calcarea carbonica

Calcarea fluorica

Causticum

Cimicifuga racemosa

Formicum acidum

Hypericum perforatum

Ledum palustre

Lithium carbonicum

Magnesia phosphorica

Phosphorus

Phytolacca decandra

Palsatilla

Rhododendron chrysanthum

Rhus toxicodendron

Ruta graveolens

Salicylicum acidum

Sepia

Zincum metallicum

Reference image arthritis.jpg

Inactive Ingredient

Bio-Energetically Enhanced, taste-free, pure water base.

Reference image arthritis.jpg

Purpose

HPUS active ingredients Purpose

Equal volumes of each ingredient in 10X, 30X, and LM1 potencies

Actaea spicata.......................rheumatic pain, jaw pain

Aesculus hippocastanum........backache, aching limbs

Arnica montana.....................body aches, back pain

Bellis perennis......................sprains, painful joints

Bryonia................................knee pain, stiff neck

Calcarea carbonica.................weak limbs, leg cramps

Calcarea fluorica....................burning pain, back pain

Causticum............................sharp pain, weakness

Cimicifuga racemosa.............restless limbs, soreness

Formicum acidum.................stiff and swollen joints

Hypericum perforatum...........nerve injury, acute pain

Ledum palustre.....................swollen ankles, ankle sprains

Lithium carbonicum...............aching joints, stiffness

Magnesia phosphorica...........leg cramps, radiating pain

Phosphorus...........................weak spine, burning pain

Phytolacca decandra.............shooting pain, stiffness

Palsatilla................................hip and joint pain

Rhododendron chrysanthum...rheumatic swelling

Rhus toxicodendron...............sore tendons and ligaments

Ruta graveolens......................contracted fingers, bone injury

Salicylicum acidum.................sciatic pain, knee pain

Sepia.....................................stiffness, back pain, restless limbs

Zincum metallicum..................numbness, trembling

Reference image arthritis.jpg

Dosage and Administration

Directions Initially, depress pump until primed. Hold close to mouth and spray one dose directly into mouth.

Adult Dose: 3 pump sprays 3 times per day. Use additionally as needed.

Children 2-12 years: 2 pumps sprays 3 times per day. Use additionally as needed.

Reference image arthritis.jpg

Indications and usage

Uses temporarily relieves symptoms due to arthritic pain:

- inflammation
- back pain
- stiff and swollen joints
- leg cramps
- rheumatic pain
- sore tendons and ligaments
- sprains and joint injuries
- bone injury
- contracted fingers
- hip and joint pain
- knee pain
- aching limbs
- sciatic pain
- restless limbs

as per various homeopathic Materia Medicas.
Reference image arthritis.jpg

Warnings

If symptoms persist or worsen, seek advice of physician. If pregnant or nursing, take only on advice of a healthcare professional. Keep out of reach of children.

Other Information

Tamper resistant for your protection. Use only if safety seal is intact.

Reference image arthritis.jpg

Keep Out Of Reach Of Children

Reference image smoke.jpg

PACKAGE LABEL

King Bio Inc.

3 Westside Drive

Asheville, NC 28806

www.kingbio.com